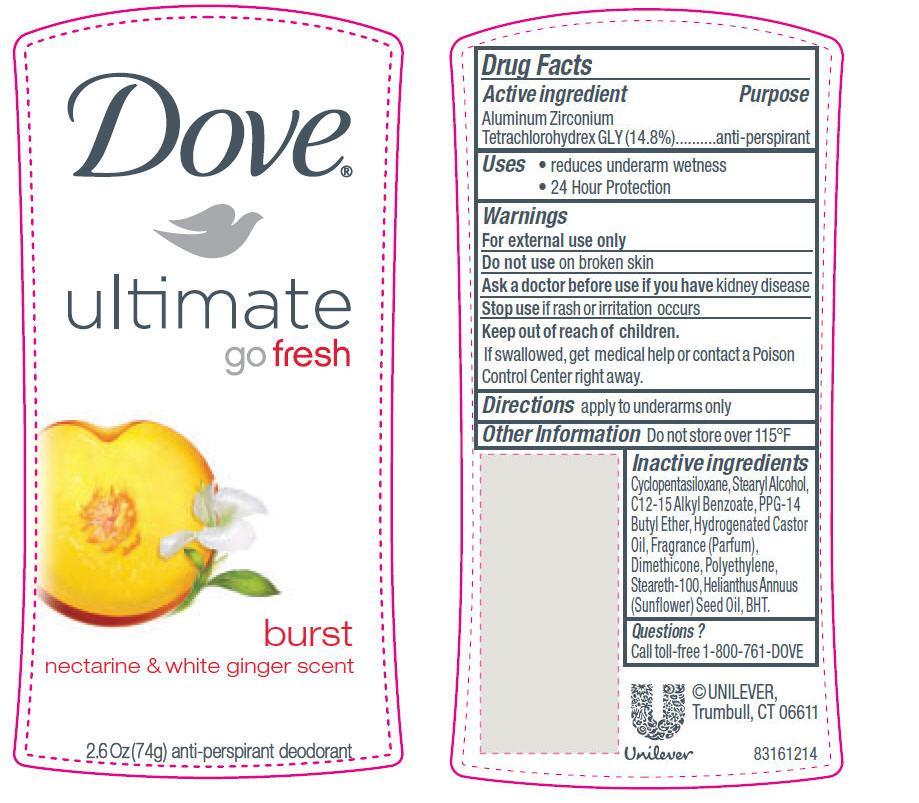 DRUG LABEL: Dove Ultimate Go Fresh Burst
NDC: 64942-1054 | Form: STICK
Manufacturer: Conopco Inc. d/b/a Unilever
Category: otc | Type: HUMAN OTC DRUG LABEL
Date: 20110526

ACTIVE INGREDIENTS: Aluminum Zirconium Tetrachlorohydrex GLY 14.8 g/100 g
INACTIVE INGREDIENTS: CYCLOMETHICONE 5; STEARYL ALCOHOL; ALKYL (C12-15) BENZOATE; PPG-14 BUTYL ETHER; HYDROGENATED CASTOR OIL; STEARETH-100; SUNFLOWER OIL; BUTYLATED HYDROXYTOLUENE

Dove Ultimate Go Fresh Burst antiperspirant deodorant

Active ingredient

Aluminum Zirconium Tetrachlorohydrex GLY(14.8%)

Purpose
antiperspirant

Uses
· reduces underarm wetness
· 24 Hour Protection

Warnings
For external use only

Do not use on broken skin

Ask a doctor before use if you have kidney disease

Stop use if rash or irritation occurs

Keep out of reach of children. If swallowed, get medical help or contact a Poison Control Center right away.

DOSAGE AND ADMINISTRATION

Directions apply to underarms only

INACTIVE INGREDIENT

Cyclopentasiloxane
Stearyl Alcohol
C12-15 Alkyl Benzoate
PPG-14 Butyl Ether
Hydrogenated Castor Oil
Fragrance (Parfum)
Dimethicone
Polyethylene
Steareth-100
Helianthus Annuus (Sunflower) Seed Oil
BHT

Questions?
Call toll-free 1-800-761-DOVE

PACKAGE LABEL

Dove UGF Burst PDP